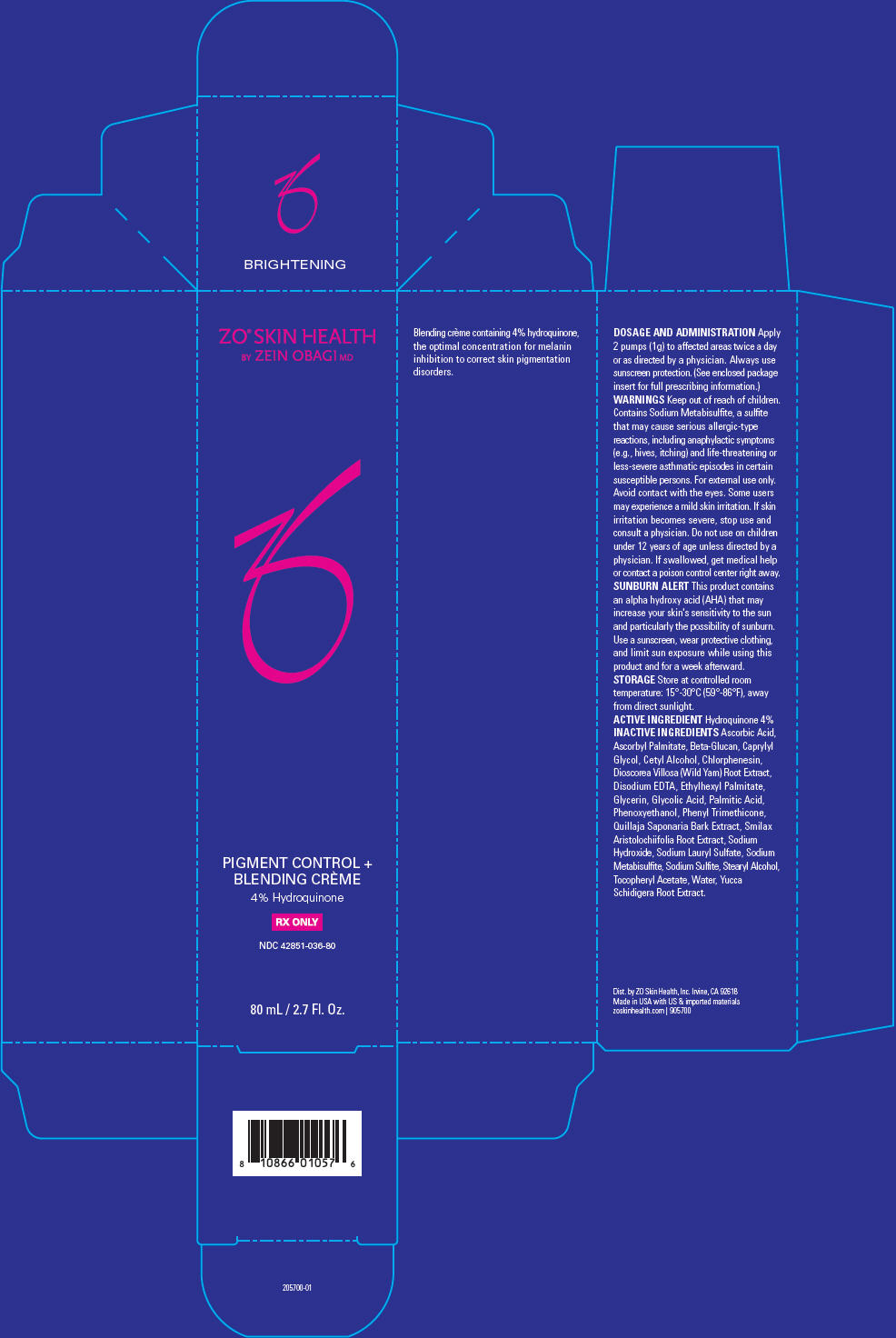 DRUG LABEL: ZO Skin Health Pigment Control Plus Blending Creme Hydroquinone
NDC: 42851-036 | Form: EMULSION
Manufacturer: ZO Skin Health, Inc.
Category: prescription | Type: HUMAN PRESCRIPTION DRUG LABEL
Date: 20220422

ACTIVE INGREDIENTS: HYDROQUINONE 0.04 g/1 mL
INACTIVE INGREDIENTS: ASCORBIC ACID; ASCORBYL PALMITATE; CAPRYLYL GLYCOL; CETYL ALCOHOL; CHLORPHENESIN; DIOSCOREA VILLOSA TUBER; EDETATE DISODIUM ANHYDROUS; ETHYLHEXYL PALMITATE; GLYCERIN; GLYCOLIC ACID; PALMITIC ACID; PHENOXYETHANOL; PHENYL TRIMETHICONE; QUILLAJA SAPONARIA BARK; SMILAX ARISTOLOCHIIFOLIA ROOT; SODIUM CHLORIDE; SODIUM HYDROXIDE; SODIUM LAURYL SULFATE; SODIUM METABISULFITE; SODIUM SULFATE; SODIUM SULFITE; STEARYL ALCOHOL; .ALPHA.-TOCOPHEROL ACETATE; WATER; YUCCA SCHIDIGERA ROOT

ZO® Skin Health Pigment Control + Blending Crème 4% Hydroquinone
National Drug Codes 42851-036-80, 42851-036-30

Blending crème containing 4% hydroquinone, the optimal concentration for melanin inhibition to correct skin pigmentation disorders.

DOSAGE AND ADMINISTRATION

Apply 2 pumps (1g) to affected areas twice a day or as directed by a physician. Always use sunscreen protection. (See enclosed package insert for full prescribing information.)

WARNINGS

Keep out of reach of children. Contains Sodium Metabisulfite, a sulfite that may cause serious allergic-type reactions, including anaphylactic symptoms (e.g., hives, itching) and life-threatening or less-severe asthmatic episodes in certain susceptible persons. For external use only. Avoid contact with the eyes. Some users may experience a mild skin irritation. If skin irritation becomes severe, stop use and consult a physician. Do not use on children under 12 years of age unless directed by a physician. If swallowed, get medical help or contact a poison control center right away.

SUNBURN ALERT

This product contains an alpha hydroxy acid (AHA) that may increase your skin's sensitivity to the sun and particularly the possibility of sunburn. Use a sunscreen, wear protective clothing, and limit sun exposure while using this product and for a week afterward.

STORAGE

Store at controlled room temperature: 15°-30°C (59°-86°F), away from direct sunlight.

ACTIVE INGREDIENT

Hydroquinone 4%

INACTIVE INGREDIENTS

Ascorbic Acid, Ascorbyl Palmitate, Beta-Glucan, Caprylyl Glycol, Cetyl Alcohol, Chlorphenesin, Dioscorea Villosa (Wild Yam) Root Extract, Disodium EDTA, Ethylhexyl Palmitate, Glycerin, Glycolic Acid, Palmitic Acid, Phenoxyethanol, Phenyl Trimethicone, Quillaja Saponaria Bark Extract, Smilax Aristolochiifolia Root Extract, Sodium Hydroxide, Sodium Lauryl Sulfate, Sodium Metabisulfite, Sodium Sulfite, Stearyl Alcohol, Tocopheryl Acetate, Water, Yucca Schidigera Root Extract.

Dist. by ZO Skin Health, Inc. Irvine, CA 92618
Made in USA with US & imported materials
zoskinhealth.com | 905700

PRINCIPAL DISPLAY PANEL - 80 mL Bottle Carton

ZO® SKIN HEALTH
BY ZEIN OBAGI MD

PIGMENT CONTROL +
BLENDING CRÈME
4% Hydroquinone

RX ONLY

NDC 42851-036-80

80 mL / 2.7 Fl. Oz.